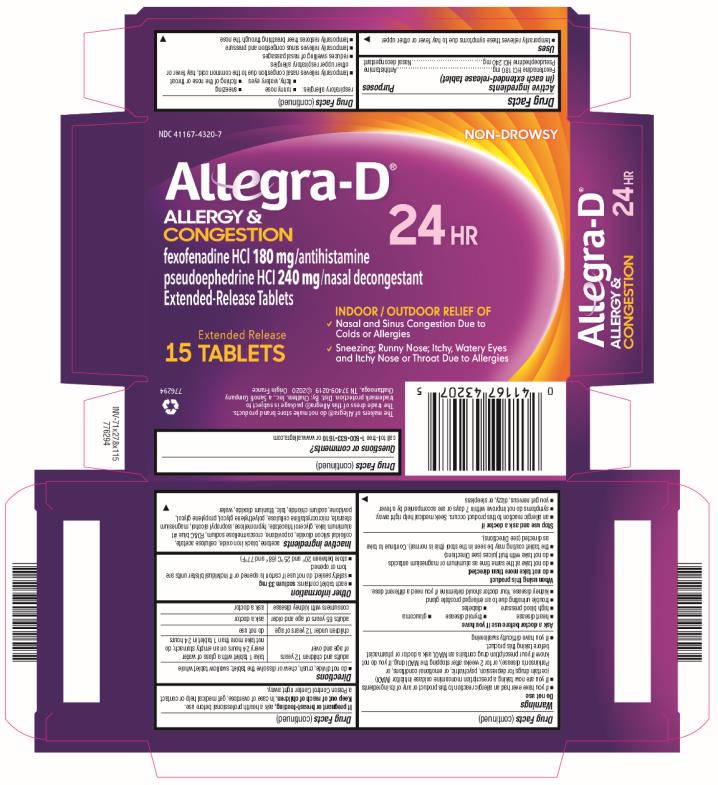 DRUG LABEL: Allegra-D Allergy and Congestion
NDC: 41167-4320 | Form: TABLET, FILM COATED, EXTENDED RELEASE
Manufacturer: Chattem, Inc.
Category: otc | Type: HUMAN OTC DRUG LABEL
Date: 20201203

ACTIVE INGREDIENTS: FEXOFENADINE HYDROCHLORIDE 180 mg/1 1; PSEUDOEPHEDRINE HYDROCHLORIDE 240 mg/1 1
INACTIVE INGREDIENTS: ALUMINUM OXIDE; TRIACETIN; ACETONE; FERROSOFERRIC OXIDE; CELLULOSE ACETATE; SILICON DIOXIDE; COPOVIDONE K25-31; CROSCARMELLOSE SODIUM; FD&C BLUE NO. 1; HYPROMELLOSES; ISOPROPYL ALCOHOL; MAGNESIUM STEARATE; CELLULOSE, MICROCRYSTALLINE; POLYETHYLENE GLYCOL, UNSPECIFIED; PROPYLENE GLYCOL; POVIDONE; SODIUM CHLORIDE; TALC; TITANIUM DIOXIDE; WATER

Allegra-D Allergy and Congestion 24 HR

Drug Facts

Active ingredients

(in each extended-release tablet)

Fexofenadine HCl 180 mg

Purpose

Antihistamine

Active ingredients

(in each extended-release tablet)

Pseudoephedrine HCl 240 mg

Purpose

Nasal decongestant

Uses

- temporarily relieves these symptoms due to hay fever or other upper respiratory allergies:
  ▪ runny nose
  ▪ sneezing
  ▪ itchy, watery eyes
  ▪ itching of the nose or throat
- temporarily relieves nasal congestion due to the common cold, hay fever or other upper respiratory allergies
- reduces swelling of nasal passages
- temporarily relieves sinus congestion and pressure
- temporarily restores freer breathing through the nose

Warnings

Do not use

- if you have ever had an allergic reaction to this product or any of its ingredients
- if you are now taking a prescription monoamine oxidase inhibitor (MAOI)
  (certain drugs for depression, psychiatric, or emotional conditions, or Parkinson’s disease), or for 2 weeks after stopping the MAOI drug. If you do not know if your prescription drug contains an MAOI, ask a doctor or pharmacist before taking this product.
- If you have difficulty swallowing

Ask a doctor before use if you have

- heart disease
- thyroid disease
- glaucoma
- high blood pressure
- diabetes
- trouble urinating due to an enlarged prostate gland
- kidney disease. Your doctor should determine if you need a different dose.

When using this product

- do not take more than directed
- do not take at the same time as aluminum or magnesium antacids
- do not take with fruit juices (see Directions)
- the tablet coating may be seen in the stool (this is normal). Continue to take as directed (see Directions).

Stop use and ask a doctor if

- an allergic reaction to this product occurs. Seek medical help right away.
- symptoms do not improve within 7 days or are accompanied by a fever
- you get nervous, dizzy, or sleepless

If pregnant or breast-feeding,

ask a health professional before use.

Keep out of reach of children.

In case of overdose, get medical help or contact a Poison Control Center right away.

Directions

- do not divide, crush, chew or dissolve the tablet; swallow tablet whole

adults and children 12 years of age and over | take 1 tablet with a glass of water every 24 hours on an empty stomach; do not take more than 1 tablet in 24 hours
children under 12 years of age | do not use
adults 65 years of age and older | ask a doctor
consumers with kidney disease | ask a doctor

Other information

- each tablet contains: sodium 33 mg
- safety sealed: do not use if carton is opened or if individual blister units are torn or opened
- store between 20º and 25ºC (68º and 77ºF)

Inactive ingredients

acetone, black iron oxide, cellulose acetate, colloidal silicon dioxide, copovidone, croscarmellose sodium, FD&C blue #1 aluminum lake, glycerol triacetate, hypromellose, isopropyl alcohol, magnesium stearate, microcrystalline cellulose, polyethylene glycol, propylene glycol, povidone, sodium chloride, talc, titanium dioxide, water

Questions or comments?

call toll-free 1-800-633-1610 or www.allegra.com

PRINCIPAL DISPLAY PANEL

NDC 41167-4320-7
NON-DROWSY
Allegra-D®
ALLERGY & CONGESTION
fexofenadine HCl 180 mg/antihistamine
pseudoephedrine HCl 240 mg/nasal decongestant
Extended Release Tablets
15 Tablets